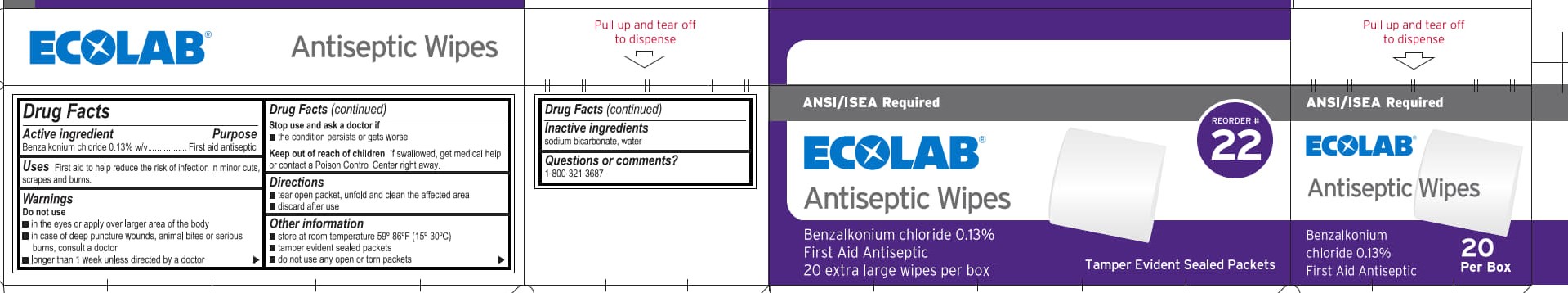 DRUG LABEL: ECOLAB Antiseptic
NDC: 71338-312 | Form: LIQUID
Manufacturer: Ecolab Food Safety Specialties, Inc.
Category: otc | Type: HUMAN OTC DRUG LABEL
Date: 20241107

ACTIVE INGREDIENTS: BENZALKONIUM CHLORIDE 1.3 mg/1 mL
INACTIVE INGREDIENTS: WATER; SODIUM BICARBONATE

Ecolab Antiseptic Wipes

Drug Facts

Active ingredient

Benzalkonium Chloride, 0.13%

Purpose

First aid antiseptic

Uses

First aid to help reduce the risk of infection in minor cuts, scrapes and burns.

Warnings

Do not use

- in the eyes or over large areas of the body
- in case of deep puncture wounds, animal bites or serious burns, consult a doctor
- longer than 1 week unless directed by a doctor

Stop use and ask a doctor if

- the condition persists or gets worse

Keep out of reach of children.

If swallowed, get medical help or contact a Poison Control Center right away.

Directions

- tear open packet, unfold and clean the affected area
- discard after use

Other information

- store at room temperature 59°-86°F (15°-30°C)
- tamper evident sealed packets
- do not use any open or torn packets

Inactive ingredients

sodium bicarbonate, water

Questions or comments?

1-800-321-3687

PACKAGE LABEL

ANSI/ISEA Required

Ecolab®

Antiseptic Wipes

Reorder # 22

Benzalkonium chloride 0.13%

First Aid Antiseptic

20 extra large wipes per box

Tamper Evident Sealed Packets